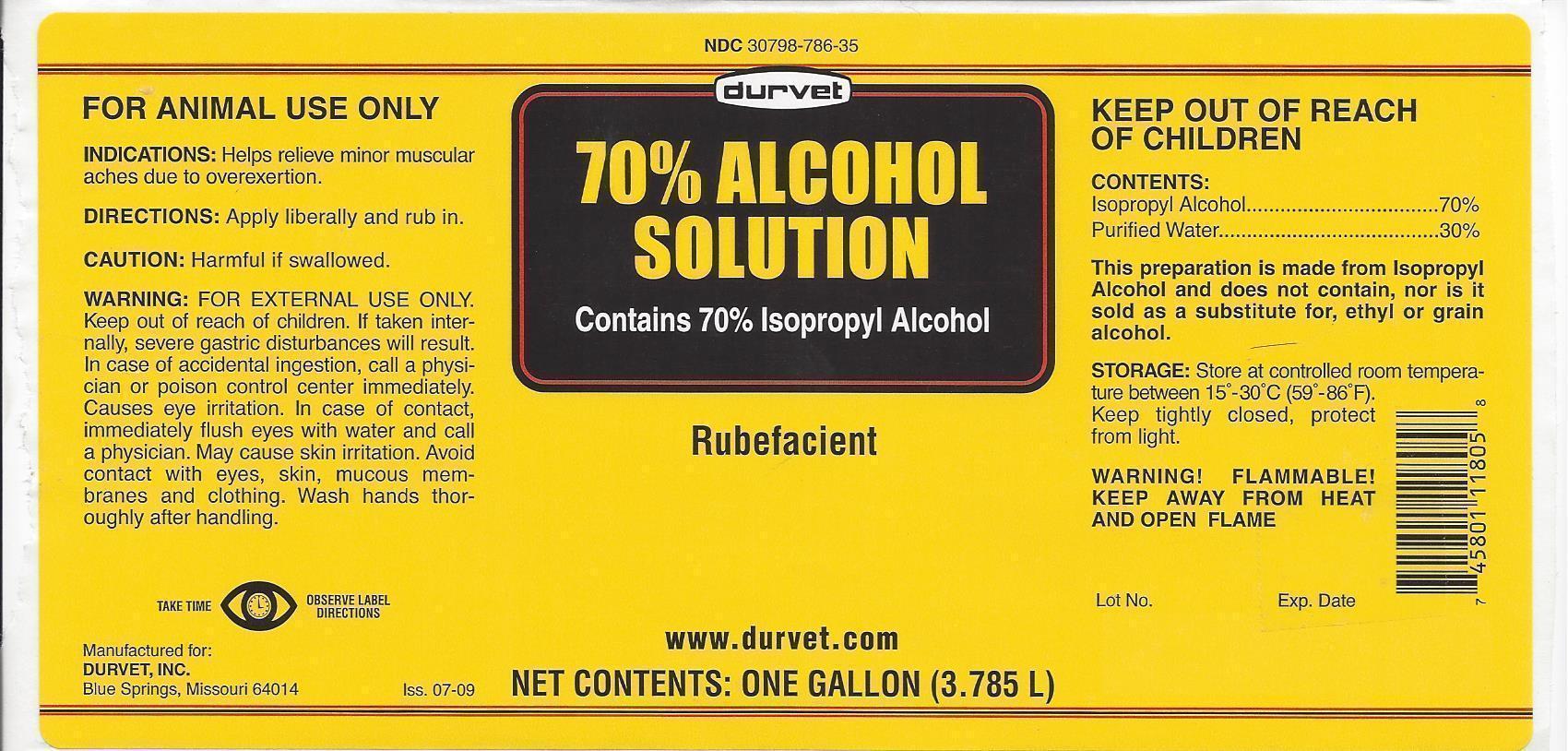 DRUG LABEL: Isopropyl Alcohol
NDC: 30798-786 | Form: LIQUID
Manufacturer: Durvet, Inc.
Category: animal | Type: OTC ANIMAL DRUG LABEL
Date: 20130920

ACTIVE INGREDIENTS: ISOPROPYL ALCOHOL 70 mL/100 mL
INACTIVE INGREDIENTS: WATER

Durvet 70% Alcohol Solution

NDC 30798-786-35 durvet 70% ALCOHOL SOLUTION Contains 70% Isopropyl Alcohol

Rubefacient

www.durvet.com

NET CONTENTS: ONE GALLON (3.785 L)

FOR ANIMAL USE ONLY

INDICATIONS: Helps relieve minor muscular aches due to overexertion.

DIRECTIONS: Apply liberally and rub in.

CAUTION:

Harmful if swallowed.

WARNING:

FOR EXTERNAL USE ONLY. Keep out of reach of children. If taken internally, severe gastric disturbances will result. In case of accidental ingestion, call a physician or poison control center immediately. Causes eye irritation. In case of contact, immediately flush eyes with water and call a physician. May cause skin irritation. Avoid contact with eyes, skin, mucous membranes and clothing. Wash hands thoroughly after handling.

TAKE TIME OBSERVE LABEL DIRECTIONS

Manufactured for:

DURVET, INC.

Blue Springs, Missouri 64014

Iss. 07-09

CONTENTS:

Isopropyl Alcohol ................ 70%

Purified Water .................... 30%

This preparation is made from Isopropyl Alcohol and does not contain, nor is it sold as a substitute for, ethyl or grain alcohol.

STORAGE:

Store at controlled room temperature between 15º - 30ºC (59º-86ºF). Keep tightly closed, protect from light.

WARNING! FLAMMABLE!

KEEP AWAY FROM HEAT AND OPEN FLAME

Lot No. Exp. Date

DESCRIPTION

Label